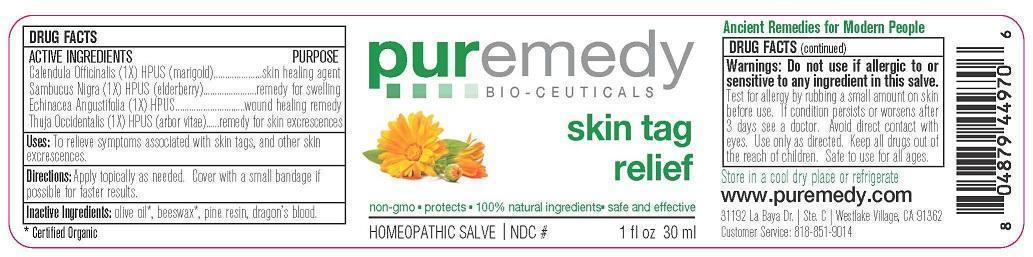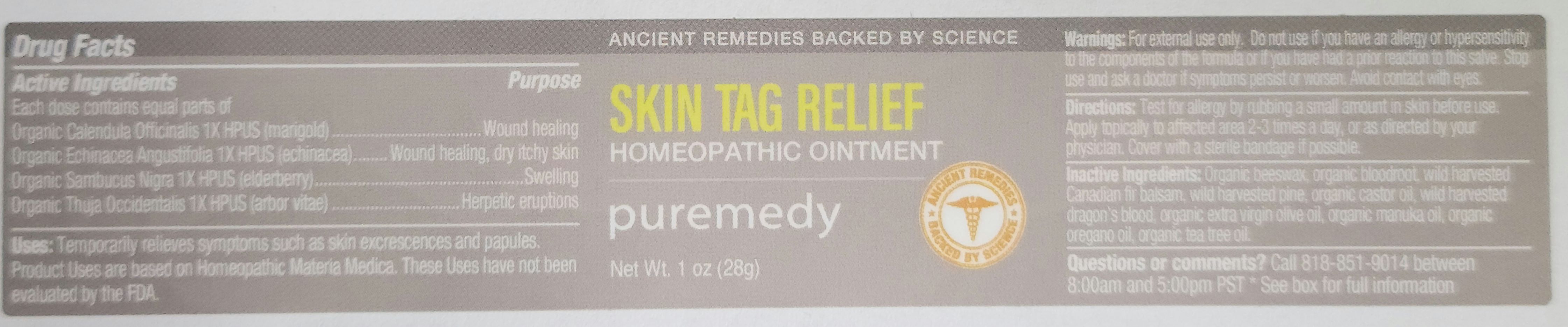 DRUG LABEL: SKIN TAG RELIEF
NDC: 52810-206 | Form: SALVE
Manufacturer: PUREMEDY
Category: homeopathic | Type: HUMAN OTC DRUG LABEL
Date: 20240111

ACTIVE INGREDIENTS: CALENDULA OFFICINALIS FLOWER 1 [hp_X]/100 mL; SAMBUCUS NIGRA FLOWER 1 [hp_X]/100 mL; ECHINACEA ANGUSTIFOLIA 1 [hp_X]/100 mL; THUJA OCCIDENTALIS LEAF 1 [hp_X]/100 mL
INACTIVE INGREDIENTS: OLIVE OIL; YELLOW WAX; PINE NEEDLE OIL (PINUS SYLVESTRIS); DRAGON'S BLOOD

SKIN TAG RELIEF (52810-206)

ACTIVE INGREDIENTS

CALENDULA OFFICINALIS (1X) HPUS) (MARIGOLD)

SAMBUCUS NIGRA (1X) HPUS (ELDER BARK AND FLOWER)

ECHINACEA ANGUSTIFOLIA (1X) HPUS (ECHINACEA)

THUJA OCCIDENTALIS (1X) HPUS (ARBOR VITAE)

PURPOSE

SKIN HEALING AGENT

REMEDY FOR SWELLING

WOUND HEALING REMEDY

REMEDY FOR SKIN EXCRESCENCES

INDICATIONS AND USAGE

USES: TO RELIEVE SYMPTOMS ASSOCIATED WITH SKIN TAGS AND OTHER SKIN EXCRESCENCES.

DOSAGE AND ADMINISTRATION

DIRECTIONS: APPLY TOPICALLY AS NEEDED. COVER WITH SMALL BANDAGE IF POSSIBLE FOR FASTER RELIEF.

INACTIVE INGREDIENT

INACTIVE INGREDIENTS: ORG. OLIVE OIL, BEESWAX, PINE RESIN, DRAGON'S BLOOD

WARNINGS

WARNINGS: DO NOT USE IF ALLERGIC TO OR SENSITIVE TO ANY INGREDIENT IN THIS SALVE. TEST FOR ALLERGY BY RUBBING A SMALL AMOUNT ON SKIN BEFORE USE. IF CONDITION PERSISTS OR WORSENS AFTER 3 DAYS SEE A DOCTOR. AVOID DIRECT CONTACT WITH EYES. USE ONLY AS DIRECTED. KEEP ALL DRUGS OUT OF USE OF CHILDREN. SAFE TO USE FOR ALL AGES.

KEEP ALL DRUGS OUT OF REACH OF CHILDREN.

STORAGE AND HANDLING

STORE IN A COOL DRY PLACE OR REFRIGERATE.

QUESTIONS

CUSTOMER SERVICE 818-851-9014